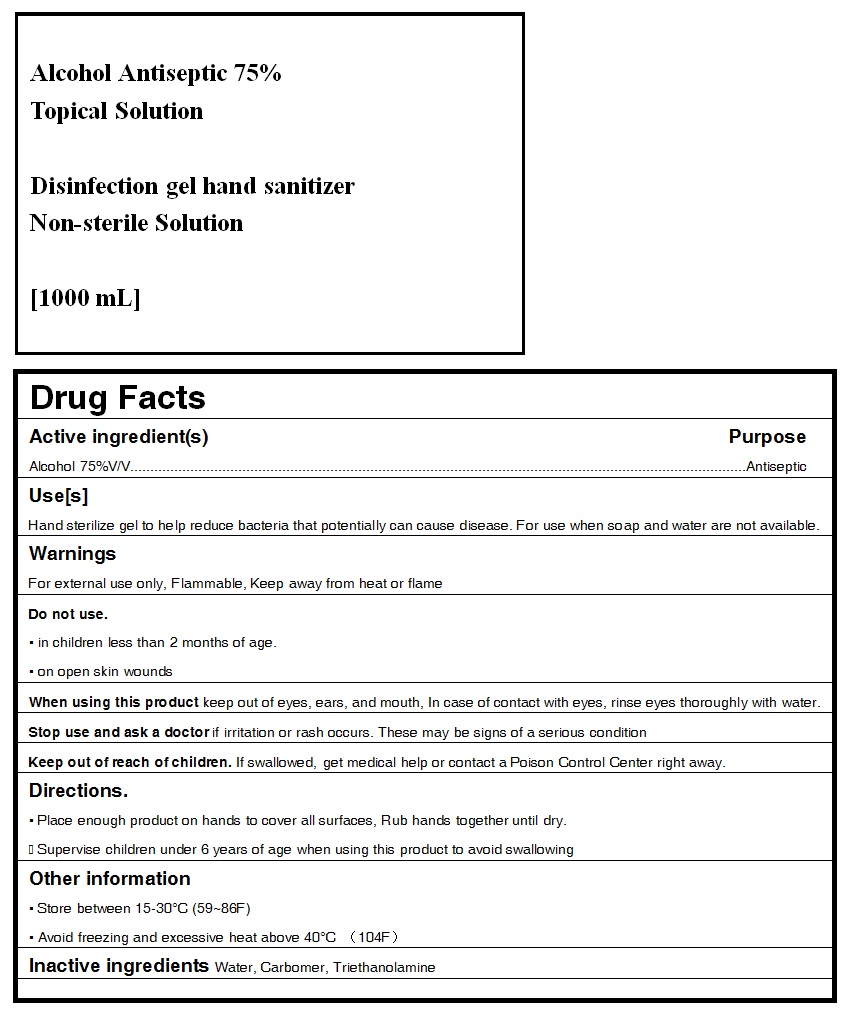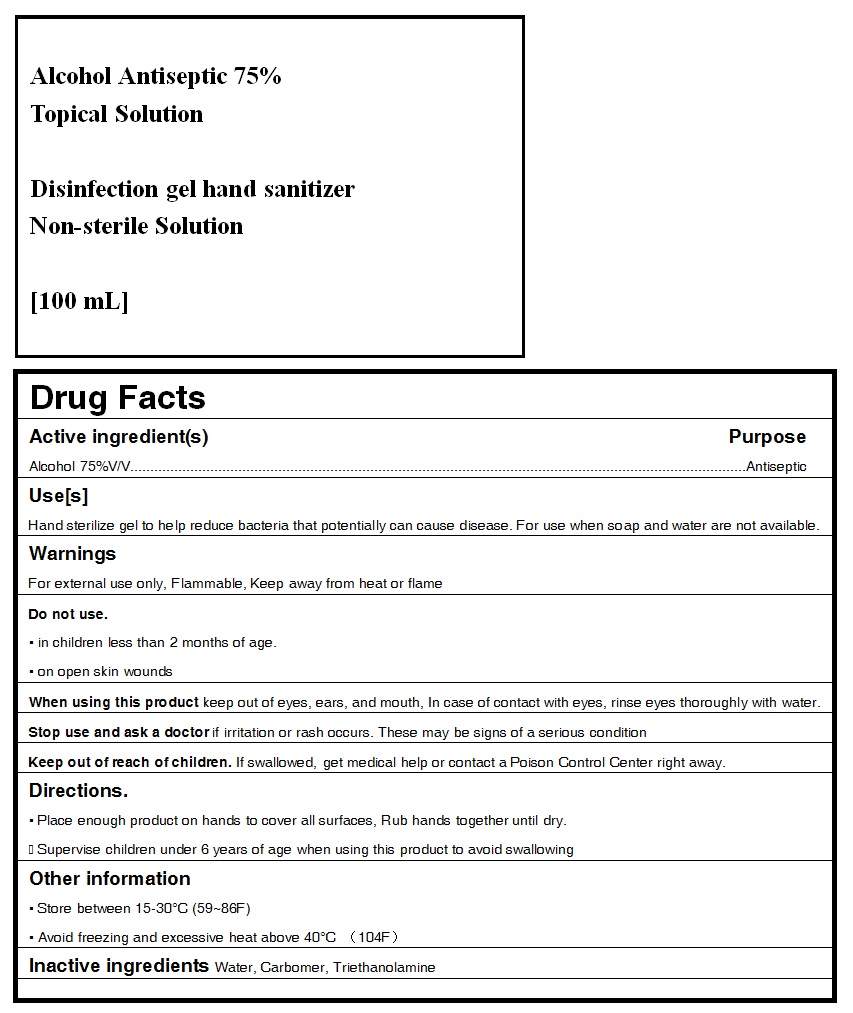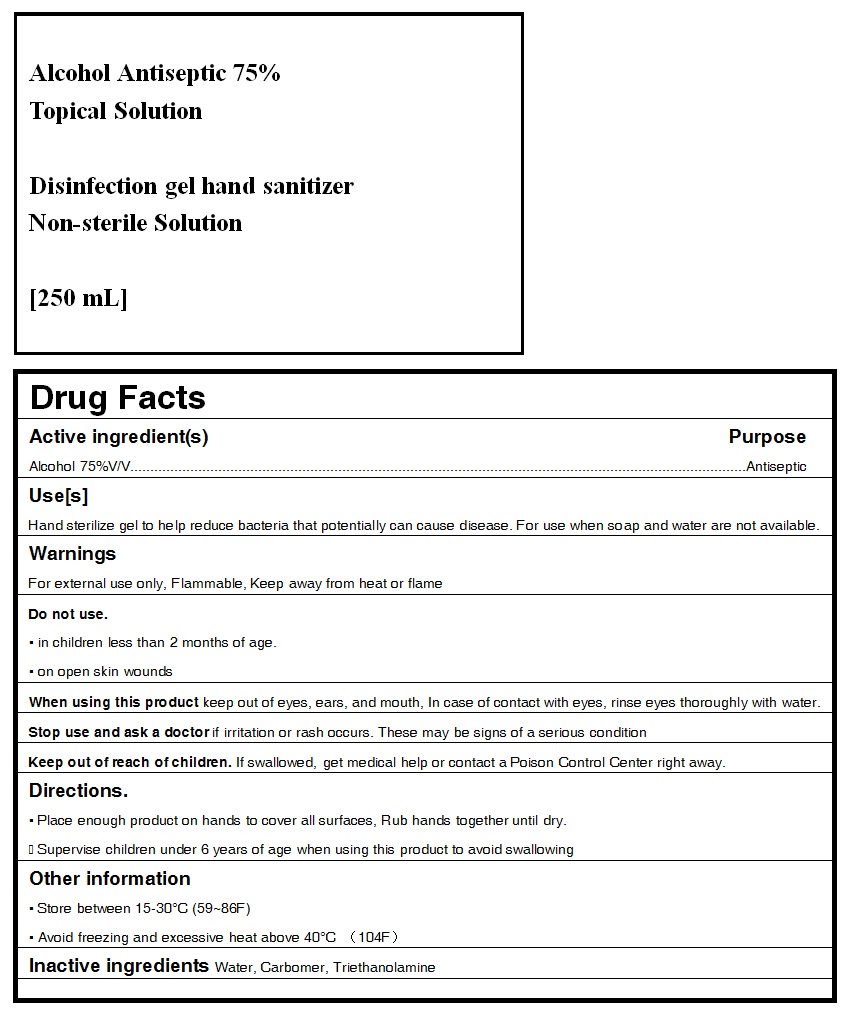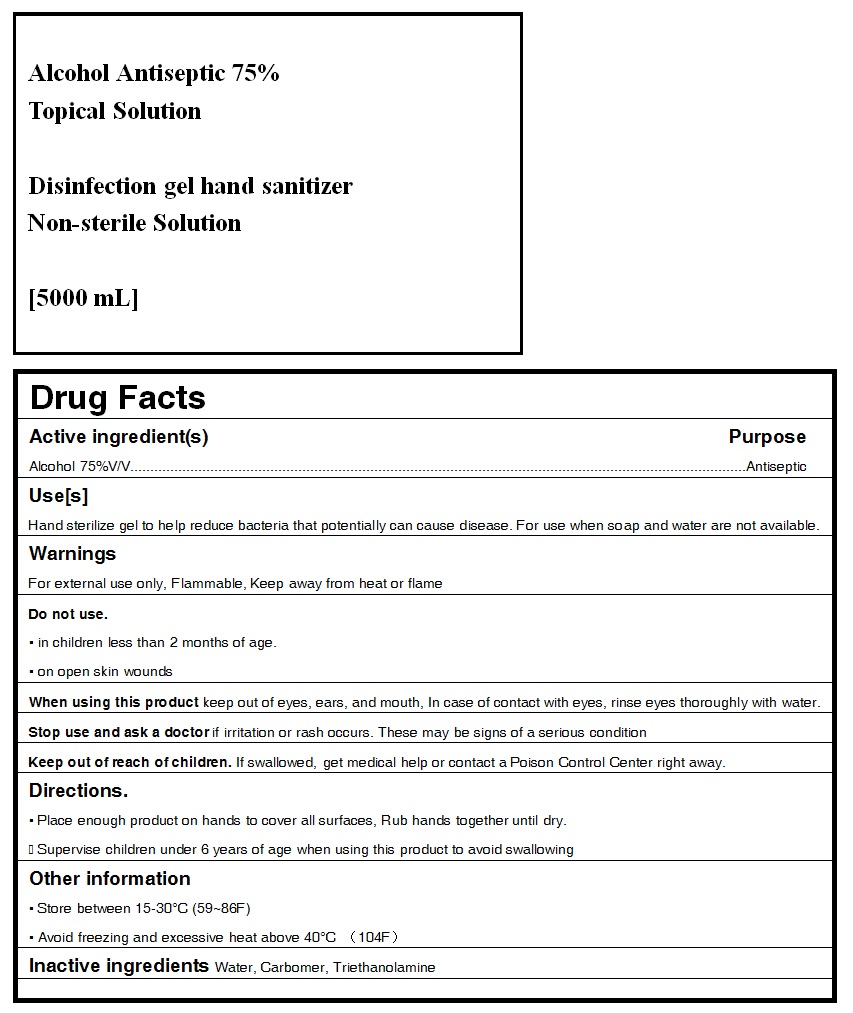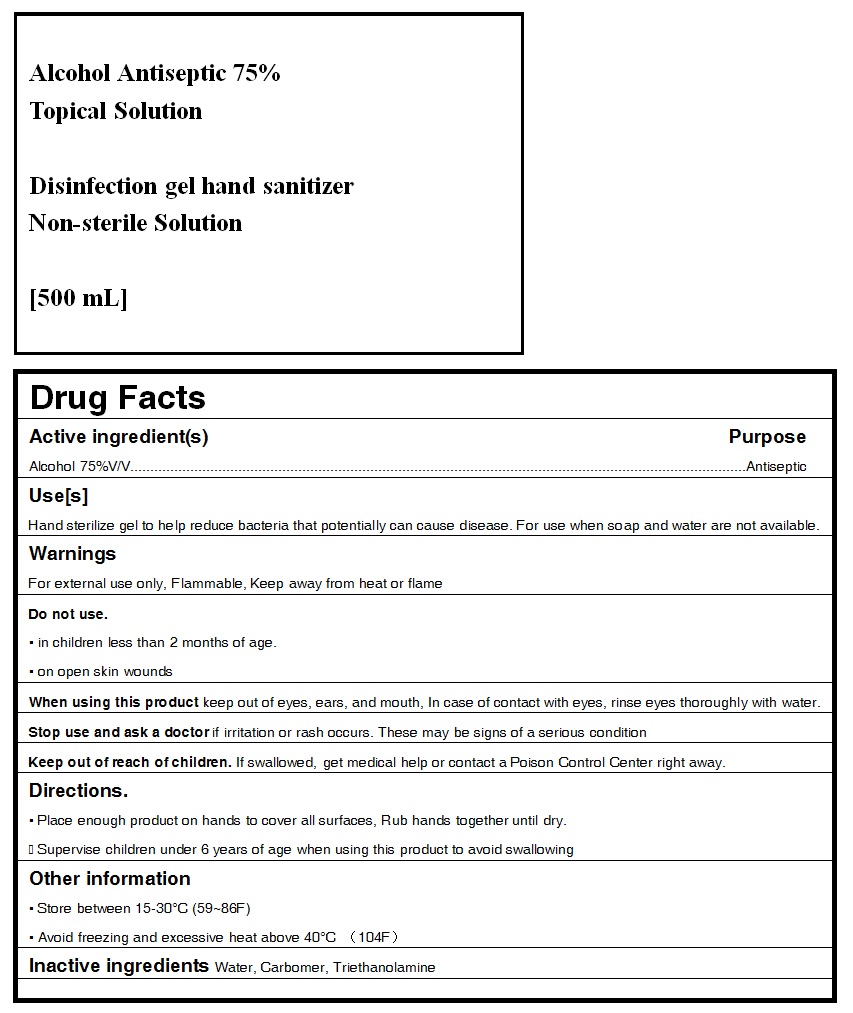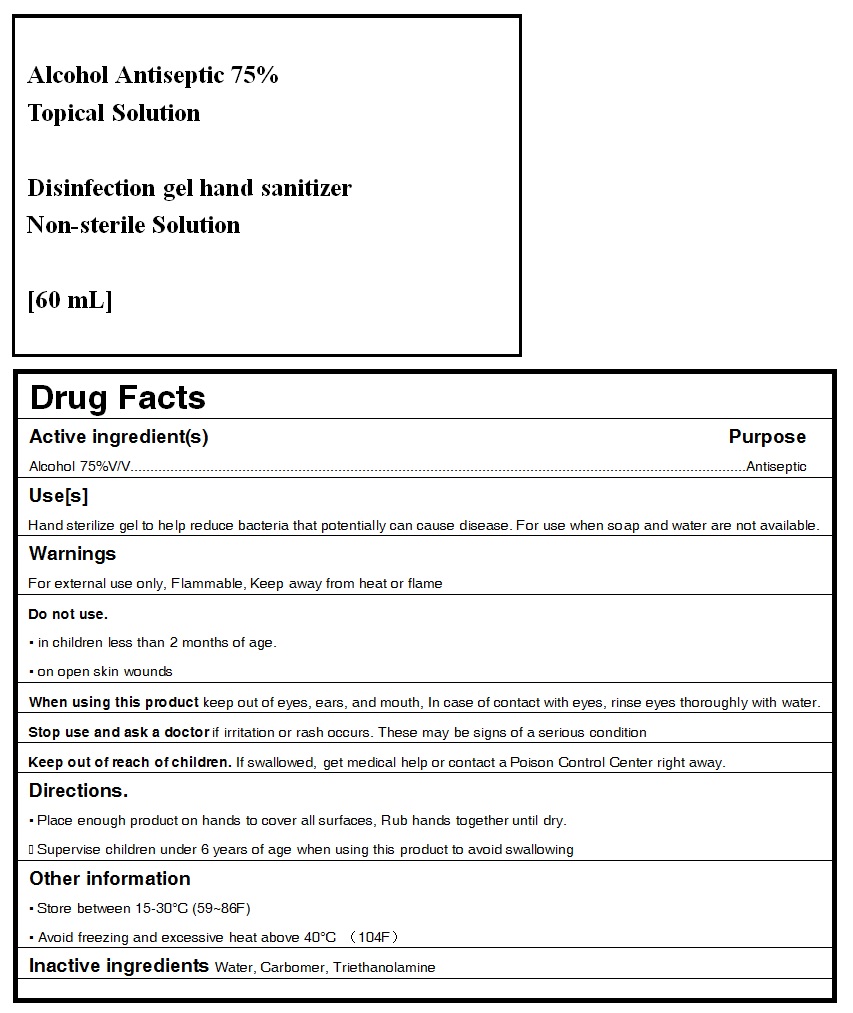 DRUG LABEL: Disinfection Gel Hand Sanitizer
NDC: 75623-001 | Form: LIQUID
Manufacturer: Zhongshan Nantao Cosmetics Co., Ltd.
Category: otc | Type: HUMAN OTC DRUG LABEL
Date: 20200416

ACTIVE INGREDIENTS: ALCOHOL 75 mL/100 mL
INACTIVE INGREDIENTS: TROLAMINE 2 mL/100 mL; CARBOMER HOMOPOLYMER, UNSPECIFIED TYPE 2 mL/100 mL; WATER 21 mL/100 mL

Active Ingredient(s)

Alcohol 75% v/v. Purpose: Antiseptic

Purpose

Antiseptic, DISINFECTION GEL HAND SANITIZER

Use

Hand sterilize gel to help reduce bacteria that potentially can cause disease. For use when soap and water are not available.

Warnings

For external use only. Flammable. Keep away from heat or flame

Do not use

- in children less than 2 months of age
- on open skin wounds

When using this product keep out of eyes, ears, and mouth. In case of contact with eyes, rinse eyes thoroughly with water.

Stop use and ask a doctor if irritation or rash occurs. These may be signs of a serious condition.

Keep out of reach of children. If swallowed, get medical help or contact a Poison Control Center right away.

Directions

- Place enough product on hands to cover all surfaces. Rub hands together until dry.
- Supervise children under 6 years of age when using this product to avoid swallowing.

Other information

- Store between 15-30C (59-86F)
- Avoid freezing and excessive heat above 40C (104F)

Inactive ingredients

Water, Carbomer, Triethanolamine

Package Label - Principal Display Panel

60 ml NDC: 75623-001-01

100 ml NDC: 75623-001-02

250 ml NDC: 75623-001-03

500 ml NDC: 75623-001-04

1000 ml NDC: 75623-001-05

5000 ml NDC: 75623-001-06